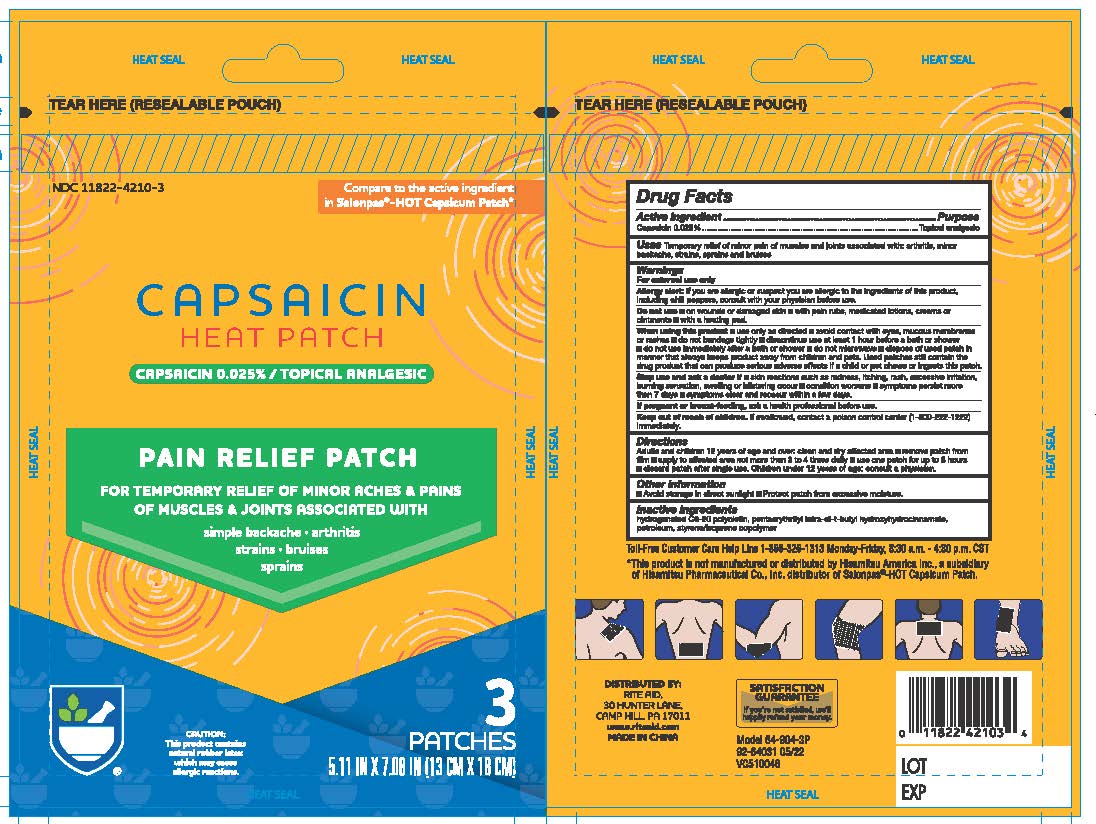 DRUG LABEL: CAPSAICIN  HEAT PATCHES PAIN RELIEF
NDC: 11822-4210 | Form: PATCH
Manufacturer: Rite Aid
Category: otc | Type: HUMAN OTC DRUG LABEL
Date: 20241218

ACTIVE INGREDIENTS: CAPSAICIN 0.025 g/100 g
INACTIVE INGREDIENTS: PENTAERYTHRITOL TETRAKIS(3-(3,5-DI-TERT-BUTYL-4-HYDROXYPHENYL)PROPIONATE); LIQUID PETROLEUM; STYRENE/ISOPRENE/STYRENE BLOCK COPOLYMER; HYDROGENATED C6-20 POLYOLEFIN (100 CST)

CAPSAICIN HEAT PATCH PAIN RELIEF PATCH

Active Ingredients

Capsaicin: 0.025%...........................Topical Analgesic

Purpose

Topical Analgesic

Uses

Temporary relief of minor pain of muscles and joints associated with:

- Arthiritis
- Minor backache
- Strains
- Sprains
- Bruises

Warnings

For External Use Only

Allergy alert

If you are allergic or suspect you are allergic to the ingredients of this product, including chill peppers, consult with your physician before use.

Do Not Use:

- On wounds or damaged skin
- with pain rubs, medicated lotions, creams, or ointments
- with heating pads

When Using this product

- Use only as directed
- Avoid contact with eyes, mucous membranes or rashes
- do not bandage tightly
- discontinue use at least 1 hour before a bath or shower
- do not use immediately after a bath or shower
- do not microwave
- dispose of used patch in a manner that always keeps products away from children and pets. Used patches still contain the drug product that can produce serious adverse effects if a child or pet chews or ingest this patch.

Stop Use and ask a doctor if:

- Skin reactions such as redness, itching, rash, excessive irritation, burning sensation, swelling or blistering occur
- Conditions worsens
- Symptoms persist more than 7 days
- Symptoms clear, and reoccur within a few days

If pregnant or breast-feeding

Ask a health professional before use

Keep Out of Reach of Children

if swallowed, contact a poison control center (1-800-222-1222) immediately.

Inactive Ingredients:

Hydrogenated Poly, Pentaerythrityl Tetra-di-t-butyl Hydroxyhydrocinnamate, Petroleum, Styrene / Isoprene Copolymer

Directions:

Adults and Children 12 Years of Age and over:

- Clean and dry affected area
- Remove patch from film
- Apply to affected area not more than 3 to 4 times daily
- use one patch for up to 8 hours
- Discard after single use
- Children under 12 years of age: consult a physician

Other Information

- Avoid storage in direct sunlight
- Protect patch from excessive moisture

Inactive Ingredients

hydrogenated C6-20 polyolefin, pentaerythrityl tetra-di-t-butyl hydroxyhydrocinnamate, petroleum, styrene/isoprene copolymer

QUESTIONS

866-326-1313 Monday - Friday 8:30 am -4:30 pm CST